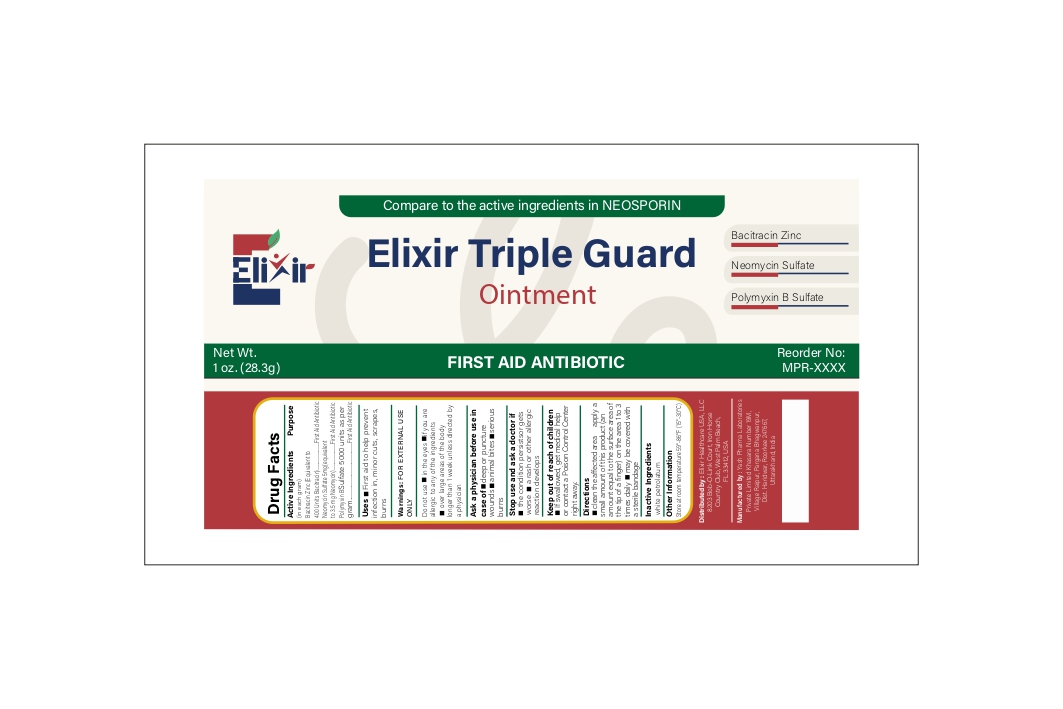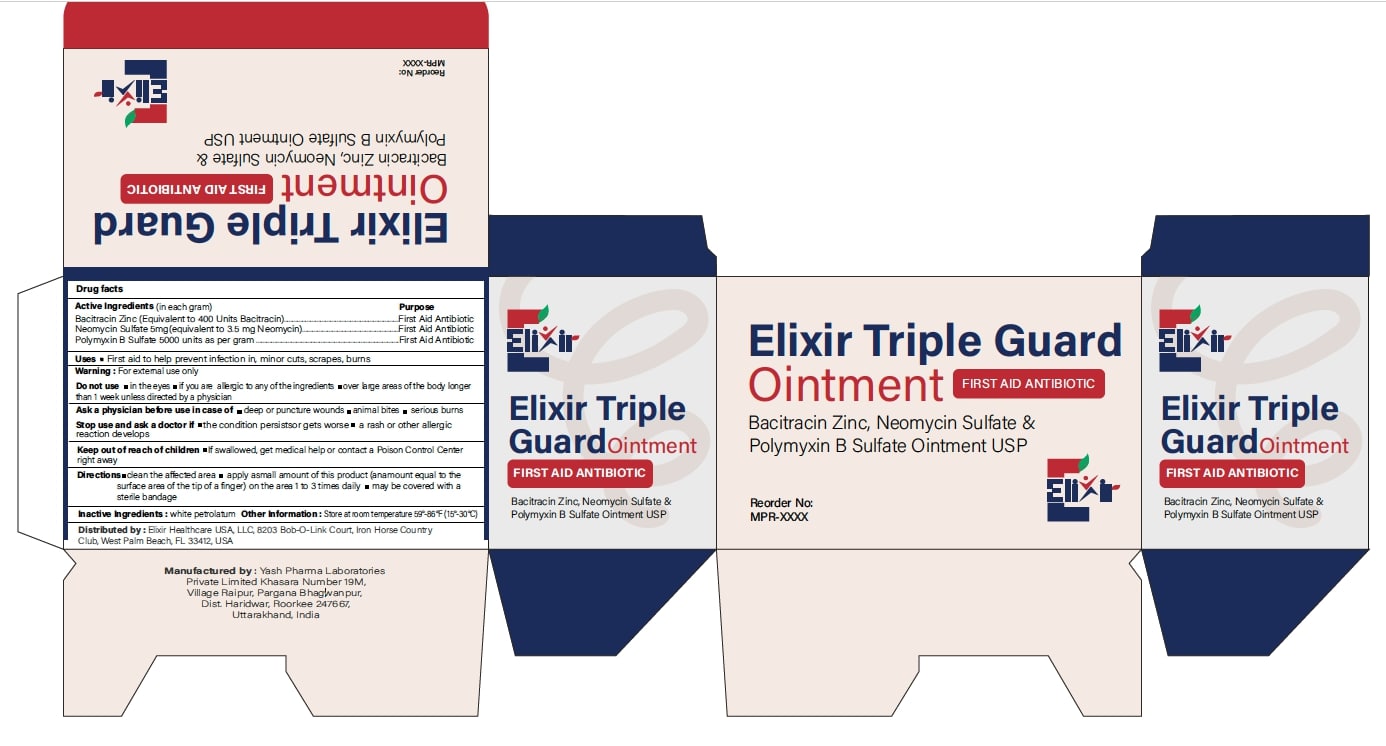 DRUG LABEL: ElixirTripleGuard
NDC: 84546-0001 | Form: OINTMENT
Manufacturer: ELIXIR HEALTHCARE USA, LLC.
Category: otc | Type: HUMAN OTC DRUG LABEL
Date: 20251213

ACTIVE INGREDIENTS: BACITRACIN ZINC 400 [USP'U]/1 g; NEOMYCIN SULFATE 3.5 mg/1 g; POLYMYXIN B SULFATE 5000 U/1 g
INACTIVE INGREDIENTS: PETROLATUM

Drug Facts

Active Ingredient (in each gram)

Bacitracin Zinc............400 units
Neomycin Sulfate 5mg (equivalent to 3.5 mg Neomycin)
Polymyxin B Sulfate ....5000 units

Purpose

First Aid Antibiotic

Uses

first aid to help prevent infection in

- minor cuts
- scrapes
- burns

Warnings

For external use only

Do not use

• in the eyes
• if you are allergic to any of the ingredients
• over large areas of the body or for longer than 1 week unless directed by a doctor

Ask a doctor before use in case of

• deep or puncture wounds
• animal bites
• serious burns

Stop use and ask a doctor if

• condition persists or gets worse
• a rash or other allergic reaction develops

Keep out of reach of children

If swallowed, get medical help or contact a Poison Control Center right away.

Directions

• Clean the affected area.
• Apply a small amount of this product (an amount equal to the surface area of the tip of a finger) 1 to 3 times daily.
• May be covered with a sterile bandage.

Inactive ingredients

white petrolatum

Other information

Store at 15°–30°C (59°–86°F). Avoid excessive heat and humidity.

PRINCIPAL DISPLAY PANEL

*Compare to the active ingredient in NEOSPORIN

NDC: 84546-0001-01

Elixir Triple Guard

Ointment

Bacitracin Zinc

Neomycin Sulfate

Polymyxin B Sulfate

First AID ANTIBIOTIC

Elixir

Net Wt. 1 oz, (28.3 gm)

Reorder No: MRP-XXXX

PRINCIPAL DISPLAY PANEL

Elixir Triple Guard

Ointment

First AID ANTIBIOTIC

Bacitracin Zinc, Neomycin Sulfate &

Polymyxin B Sulfate Ointment USP

Net Wt. 0.9G, (144 Packets)

Reorder No: MRP-XXXX